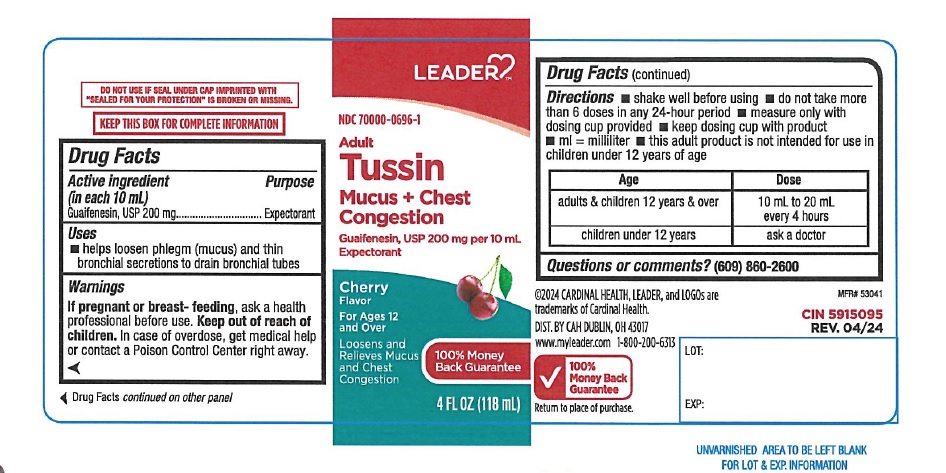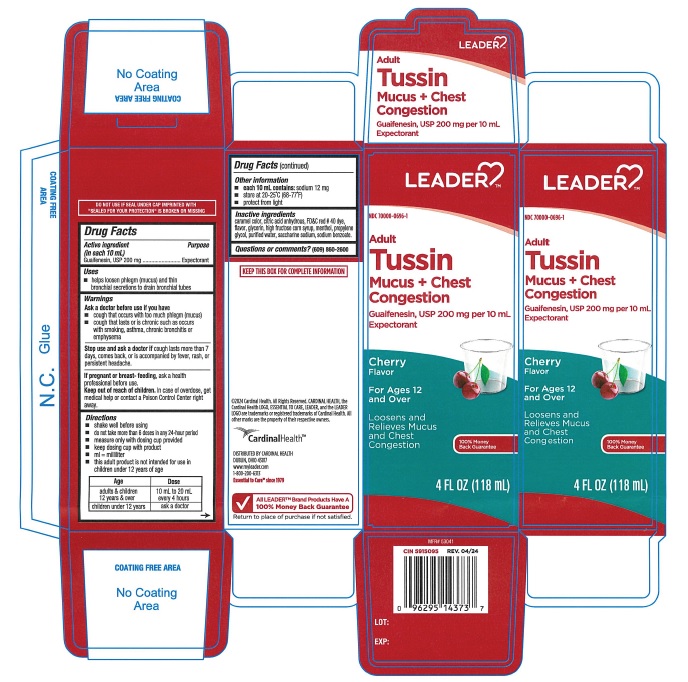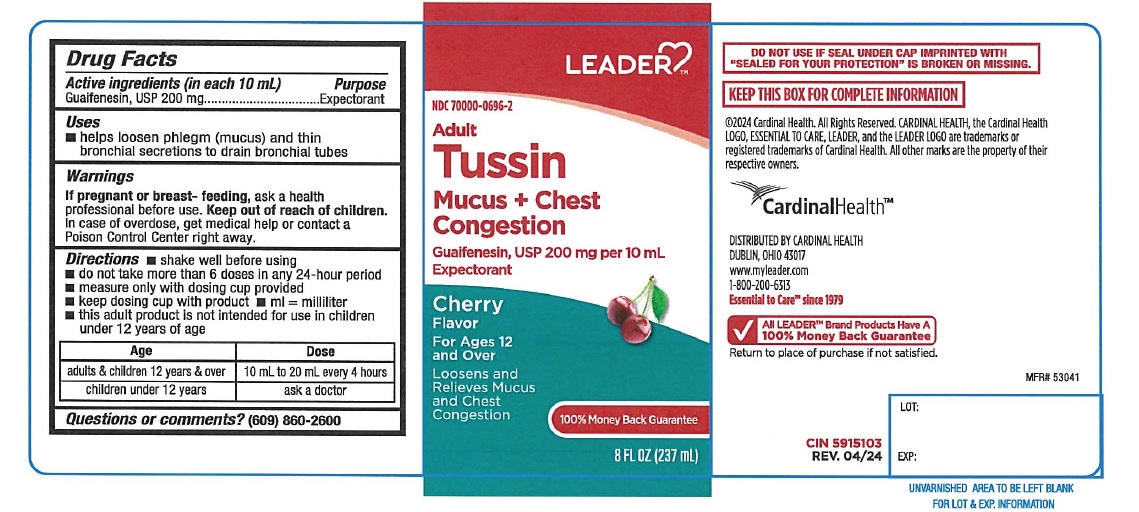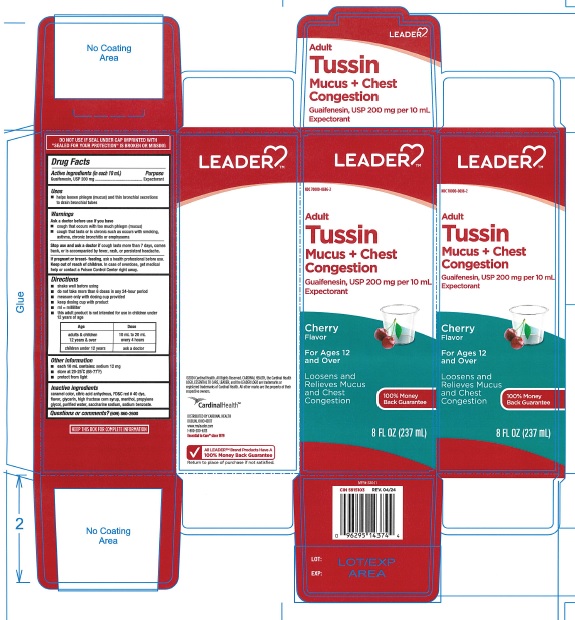 DRUG LABEL: Leader  Adult Tussin  Mucus and Chest Congestion 541
NDC: 70000-0696 | Form: LIQUID
Manufacturer: CARDINAL HEALTH 110, LLC. DBA LEADER
Category: otc | Type: Human OTC Drug Label
Date: 20240920

ACTIVE INGREDIENTS: GUAIFENESIN 200 mg/10 mL
INACTIVE INGREDIENTS: ANHYDROUS CITRIC ACID; FD&C RED NO. 40; GLYCERIN; MENTHOL; HIGH FRUCTOSE CORN SYRUP; PROPYLENE GLYCOL; WATER; SACCHARIN SODIUM; SODIUM BENZOATE; CARAMEL

Leader Adult Tussin Mucus and Chest Congestion 541

ACTIVE INGREDIENT(S)

Guaifenesin, USP 200 mg

PURPOSE

Expectorant

USE(S)

- helps loosen phlegm(mucus) and thin bronchial secretions to drain bronchial tubes

WARNINGS

.

ASK A DOCTOR BEFORE USE IF YOU HAVE

- cough that occurs with too much phlegm(mucus)
- cough that lasts or is chronic such as occurs with smoking, asthma, chronic bronchitis or emphysema

STOP USE AND ASK DOCTOR IF

cough lasts more than 7 days, comes back, or is accompanied by fever, rash, or persistent headache.

IF PREGNANT OR BREAST-FEEDING,

ask a health professional before use.

KEEP OUT OF REACH OF CHILDREN

In case of overdose, get medical help or contact a Poison Control Center right away.

DIRECTIONS

shake well before using

do not take more than 6 doses in any 24-hour period

measure only with dosing cup provided

keep dosing cup with product

ml=milliliter

this adult product is not intended for use in children under 12 years of age

Age | Dose
adults & children 12 years & over | 10 mL to 20 mL every 4 hours
children under 12 years | ask a doctor

OTHER INFORMATION

- each 10 mL contains: sodium 12 mg
- store at 20-25oC(68-77oF)
- protect from light

INACTIVE INGRADIENTS

caramel color, citric acid anhydrous, FD&C red# 40 dye, flavor, glycerin, high fructose corn syrup, menthol, propylene glycol, purified water, saccharine sodium, sodium benzoate.

QUESTIONS OR COMMENTS?

(609) 860-2600

PRINCIPAL DISPLAY PANEL

LEADER TM

NDC70000-0696-1

Adult Tussin

Mucus + Chest Congestion

Guaifenesin, USP 200 mg per 10 mL

Expectorant

Cherry Flavor

For Ages 12 and Over

Loosens and Relieves Mucus and

Chest Congestion

100% Money Back Guarantee

4FL OZ(118 mL)

LEADER TM

NDC70000-0696-2

Adult Tussin

Mucus + Chest Congestion

Guaifenesin, USP 200 mg per 10 mL

Expectorant

Cherry Flavor

For Ages 12 and Over

Loosens and Relieves Mucus and

Chest Congestion

100% Money Back Guarantee

8FL OZ (237 mL)